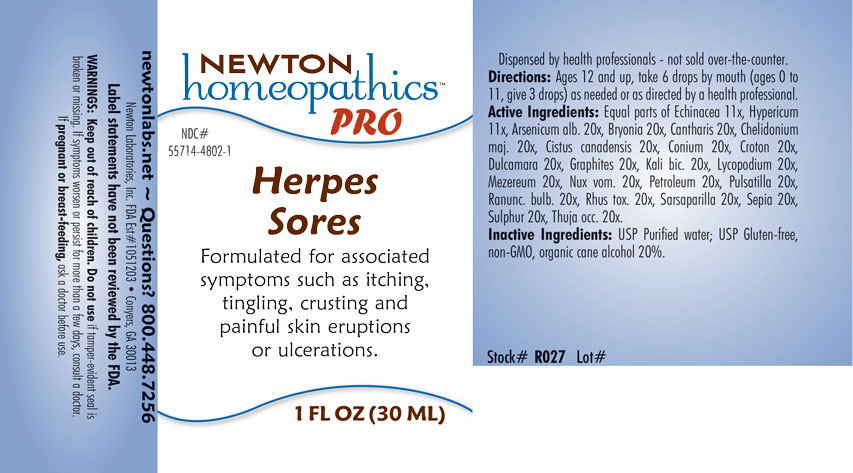 DRUG LABEL: Herpes Sores
NDC: 55714-4802 | Form: LIQUID
Manufacturer: Newton Laboratories, Inc.
Category: homeopathic | Type: HUMAN OTC DRUG LABEL
Date: 20201203

ACTIVE INGREDIENTS: ARSENIC TRIOXIDE 20 [hp_X]/1 mL; BRYONIA ALBA ROOT 20 [hp_X]/1 mL; LYTTA VESICATORIA 20 [hp_X]/1 mL; CHELIDONIUM MAJUS 20 [hp_X]/1 mL; HELIANTHEMUM CANADENSE 20 [hp_X]/1 mL; CONIUM MACULATUM FLOWERING TOP 20 [hp_X]/1 mL; CROTON TIGLIUM SEED 20 [hp_X]/1 mL; SOLANUM DULCAMARA TOP 20 [hp_X]/1 mL; GRAPHITE 20 [hp_X]/1 mL; POTASSIUM DICHROMATE 20 [hp_X]/1 mL; LYCOPODIUM CLAVATUM SPORE 20 [hp_X]/1 mL; DAPHNE MEZEREUM BARK 20 [hp_X]/1 mL; STRYCHNOS NUX-VOMICA SEED 20 [hp_X]/1 mL; KEROSENE 20 [hp_X]/1 mL; ANEMONE PULSATILLA 20 [hp_X]/1 mL; RANUNCULUS BULBOSUS 20 [hp_X]/1 mL; TOXICODENDRON PUBESCENS LEAF 20 [hp_X]/1 mL; SMILAX ORNATA ROOT 20 [hp_X]/1 mL; HYPERICUM PERFORATUM 11 [hp_X]/1 mL; SEPIA OFFICINALIS JUICE 20 [hp_X]/1 mL; SULFUR 20 [hp_X]/1 mL; THUJA OCCIDENTALIS LEAFY TWIG 20 [hp_X]/1 mL; ECHINACEA, UNSPECIFIED 11 [hp_X]/1 mL
INACTIVE INGREDIENTS: ALCOHOL; WATER

Herpes 4802L

INDICATIONS & USAGE SECTION

Formulated for associated symptoms such as itching, tingling, crusting and painful skin eruptions or ulcerations.

DOSAGE & ADMINISTRATION SECTION

Directions: Ages 12 and up, take 6 drops by mouth (ages 0 to 11, give 3 drops) as needed or as directed by a health professional.

OTC - ACTIVE INGREDIENT SECTION

Equal parts of Echinacea 11x, Hypericum perforatum 11x, Arsenicum album 20x, Bryonia 20x, Cantharis 20x, Chelidonium majus 20x, Cistus canadensis 20x, Conium maculatum 20x, Croton tiglium 20x, Dulcamara 20x, Graphites 20x, Kali bichromicum 20x, Lycopodium clavatum 20x, Mezereum 20x, Nux vomica 20x, Petroleum 20x, Pulsatilla 20x, Ranunculus bulbosus 20x, Rhus toxicodendron 20x, Sarsaparilla 20x, Sepia 20x, Sulphur 20x, Thuja occidentalis 20x.

OTC - PURPOSE SECTION

Formulated for associated symptoms such as itching, tingling,crusting and painful skin eruptions or ulcerations.

INACTIVE INGREDIENT SECTION

Inactive Ingredients: USP Purified Water; USP Gluten-free, non-GMO, organic cane alcohol 20%.

QUESTIONS SECTION

newtonlabs.net – Questions? 800.448.7256

Newton Laboratories, Inc. FDA Est # 1051203 - Conyers, GA 30013

WARNINGS SECTION

WARNINGS: Keep out of reach of children. Do not use if tamper-evident seal is broken or missing. If symptoms worsen or persist for more than a few days, consult a doctor. If pregnant or breast-feeding, ask a doctor before use.

OTC - PREGNANCY OR BREAST FEEDING SECTION

If pregnant or breast-feeding, ask a doctor before use.

OTC - KEEP OUT OF REACH OF CHILDREN SECTION

Keep out of reach of children.